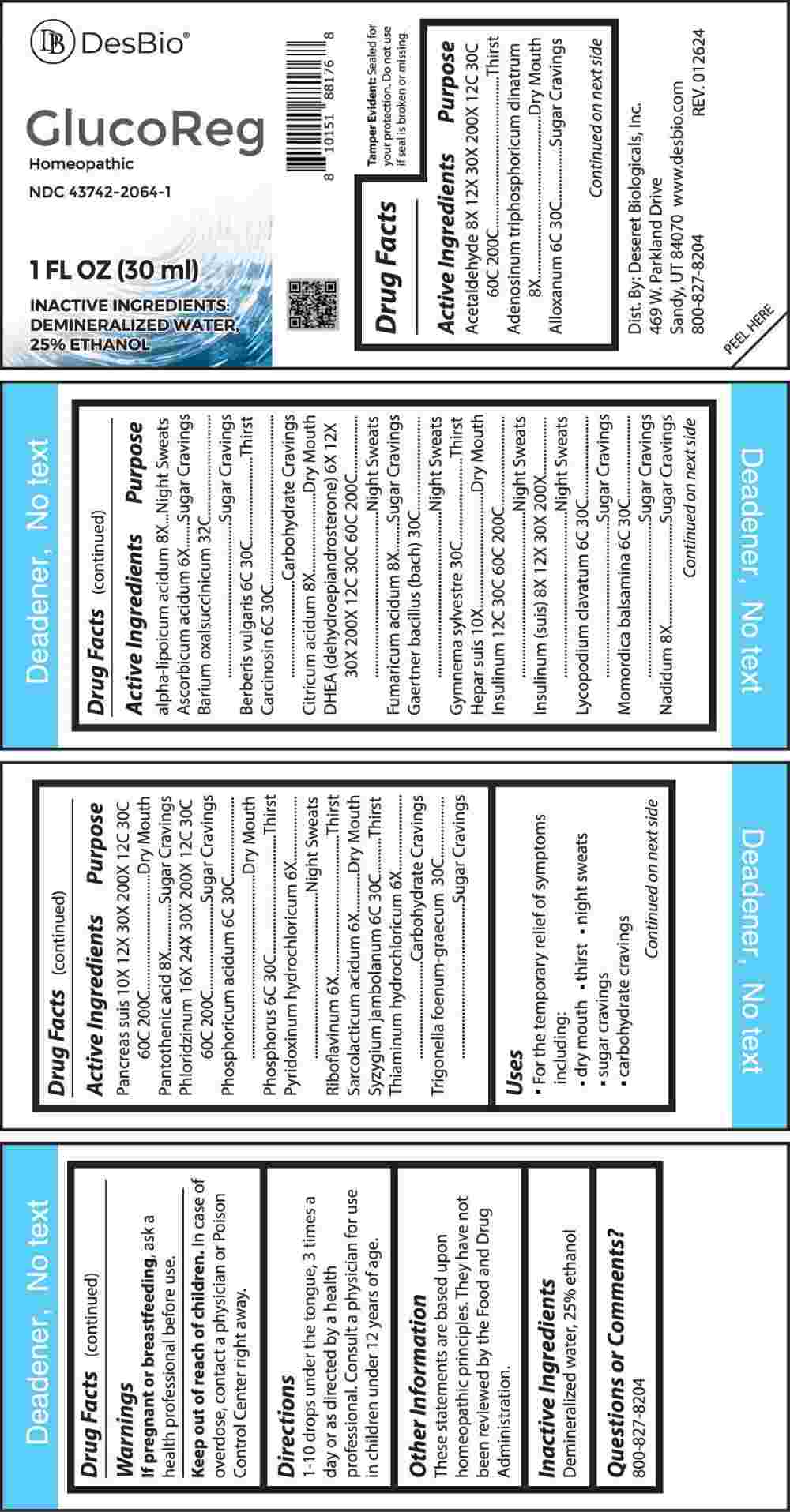 DRUG LABEL: Glucoreg
NDC: 43742-2064 | Form: LIQUID
Manufacturer: Deseret Biologicals, Inc.
Category: homeopathic | Type: HUMAN OTC DRUG LABEL
Date: 20240429

ACTIVE INGREDIENTS: ASCORBIC ACID 6 [hp_X]/1 mL; PYRIDOXINE HYDROCHLORIDE 6 [hp_X]/1 mL; RIBOFLAVIN 6 [hp_X]/1 mL; LACTIC ACID, L- 6 [hp_X]/1 mL; THIAMINE HYDROCHLORIDE 6 [hp_X]/1 mL; PRASTERONE 6 [hp_X]/1 mL; ADENOSINE TRIPHOSPHATE DISODIUM 8 [hp_X]/1 mL; THIOCTIC ACID 8 [hp_X]/1 mL; ANHYDROUS CITRIC ACID 8 [hp_X]/1 mL; FUMARIC ACID 8 [hp_X]/1 mL; NADIDE 8 [hp_X]/1 mL; PANTOTHENIC ACID 8 [hp_X]/1 mL; ACETALDEHYDE 8 [hp_X]/1 mL; INSULIN PORK 8 [hp_X]/1 mL; INSULIN HUMAN 12 [hp_C]/1 mL; PORK LIVER 10 [hp_X]/1 mL; SUS SCROFA PANCREAS 10 [hp_X]/1 mL; PHLORIZIN 16 [hp_X]/1 mL; ALLOXAN 6 [hp_C]/1 mL; BERBERIS VULGARIS ROOT BARK 6 [hp_C]/1 mL; HUMAN BREAST TUMOR CELL 6 [hp_C]/1 mL; LYCOPODIUM CLAVATUM SPORE 6 [hp_C]/1 mL; MOMORDICA BALSAMINA IMMATURE FRUIT 6 [hp_C]/1 mL; PHOSPHORIC ACID 6 [hp_C]/1 mL; PHOSPHORUS 6 [hp_C]/1 mL; SYZYGIUM CUMINI SEED 6 [hp_C]/1 mL; SALMONELLA ENTERICA SUBSP. ENTERICA SEROVAR ENTERITIDIS 30 [hp_C]/1 mL; GYMNEMA SYLVESTRE LEAF 30 [hp_C]/1 mL; TRIGONELLA FOENUM-GRAECUM WHOLE 32 [hp_C]/1 mL; BARIUM OXALOSUCCINATE 32 [hp_C]/1 mL
INACTIVE INGREDIENTS: WATER; ALCOHOL

DRUG FACTS:

ACTIVE INGREDIENTS:

Acetaldehyde 8X, 12X, 30X, 200X, 12C, 30C, 60C, 200C, Adenosinum Triphosphoricum Dinatrum 8X, Alloxanum 6C, 30C, Alpha-Lipoicum Acidum 8X, Ascorbic Acid 6X, Barium Oxalsuccinicum 32C, Berberis Vulgaris 6C, 30C, Carcinosin 6C, 30C, Citricum Acidum 8X, DHEA (Dehydroepiandrosterone) 6X, 12X, 30X, 200X, 12C, 30C, 60C, 200C, Fumaricum Acidum 8X, Gaertner Bacillus (Bach) 30C, Gymnema Sylvestre 30C, Hepar Suis 10X, Insulinum 12C, 30C, 60C, 200C, Insulinum (Suis) 8X, 12X, 30X, 200X, Lycopodium Clavatum 6C, 30C, Momordica Balsamina 6C, 30C, Nadidum 8X, Pancreas Suis 10X, 12X, 30X, 200X, 12C, 30C, 60C, 200C, Pantothenic Acid 8X, Phloridzinum 16X, 24X, 30X, 200X, 12C, 30C, 60C, 200C, Phosphoricum Acidum 6C, 30C, Phosphorus 6C, 30C, Pyridoxinum Hydrochloricum 6X, Riboflavinum 6X, Sarcolacticum Acidum 6X, Syzygium Jambolanum 6C, 30C, Thiaminum Hydrochloricum 6X, Trigonella Foenum-Graecum 30C.

PURPOSE:

Acetaldehyde - Thirst, Adenosinum Triphosphoricum Dinatrum – Dry Mouth, Alloxanum – Sugar Cravings, Alpha-Lipoicum Acidum – Night Sweats, Ascorbic Acid – Sugar Cravings, Barium Oxalsuccinicum – Sugar Cravings, Berberis Vulgaris - Thirst, Carcinosin – Carbohydrate Cravings, Citricum Acidum – Dry Mouth, DHEA (Dehydroepiandrosterone) – Night Sweats, Fumaricum Acidum – Sugar Cravings, Gaertner Bacillus (Bach) – Night Sweats, Gymnema Sylvestre - Thirst, Hepar Suis – Dry Mouth, Insulinum – Night Sweats, Insulinum (Suis) – Night Sweats, Lycopodium Clavatum – Sugar Cravings, Momordica Balsamina – Sugar Cravings, Nadidum – Sugar Cravings, Pancreas Suis – Dry Mouth, Pantothenic Acid – Sugar Cravings, Phloridzinum – Sugar Cravings, Phosphoricum Acidum – Dry Mouth, Phosphorus - Thirst, Pyridoxinum Hydrochloricum – Night Sweats, Riboflavinum - Thirst, Sarcolacticum Acidum – Dry Mouth, Syzygium Jambolanum - Thirst, Thiaminum Hydrochloricum – Carbohydrate Cravings, Trigonella Foenum-Graecum – Sugar Cravings

USES:

• For the temporary relief of symptoms including:

• dry mouth • thirst • night sweats • sugar cravings • carbohydrate cravings

These statements are based upon homeopathic principles. They have not been reviewed by the Food and Drug Administration.

WARNINGS:

If pregnant or breast-feeding, ask a health professional before use.

Keep out of reach of children. In case of overdose, contact a physician or Poison Control Center right away.

Tamper Evident: Sealed for your protection. Do not use if seal is broken or missing.

KEEP OUT OF REACH OF CHILDREN:

In case of overdose, contact a physician or Poison Control Center right away.

DIRECTIONS:

1-10 drops under the tongue, 3 times a day or as directed by a health professional. Consult a physician for use in children under 12 years of age.

INACTIVE INGREDIENTS:

Demineralized water, 25% ethanol

QUESTIONS:

Dist. By: Deseret Biologicals, Inc.
469 W. Parkland Drive
Sandy, UT 84070

www.desbio.com

800-827-8204

PACKAGE LABEL DISPLAY:

Des Bio

GlucoReg

Homeopathic
NDC 43742-2064-1
1 FL OZ (30 ml)